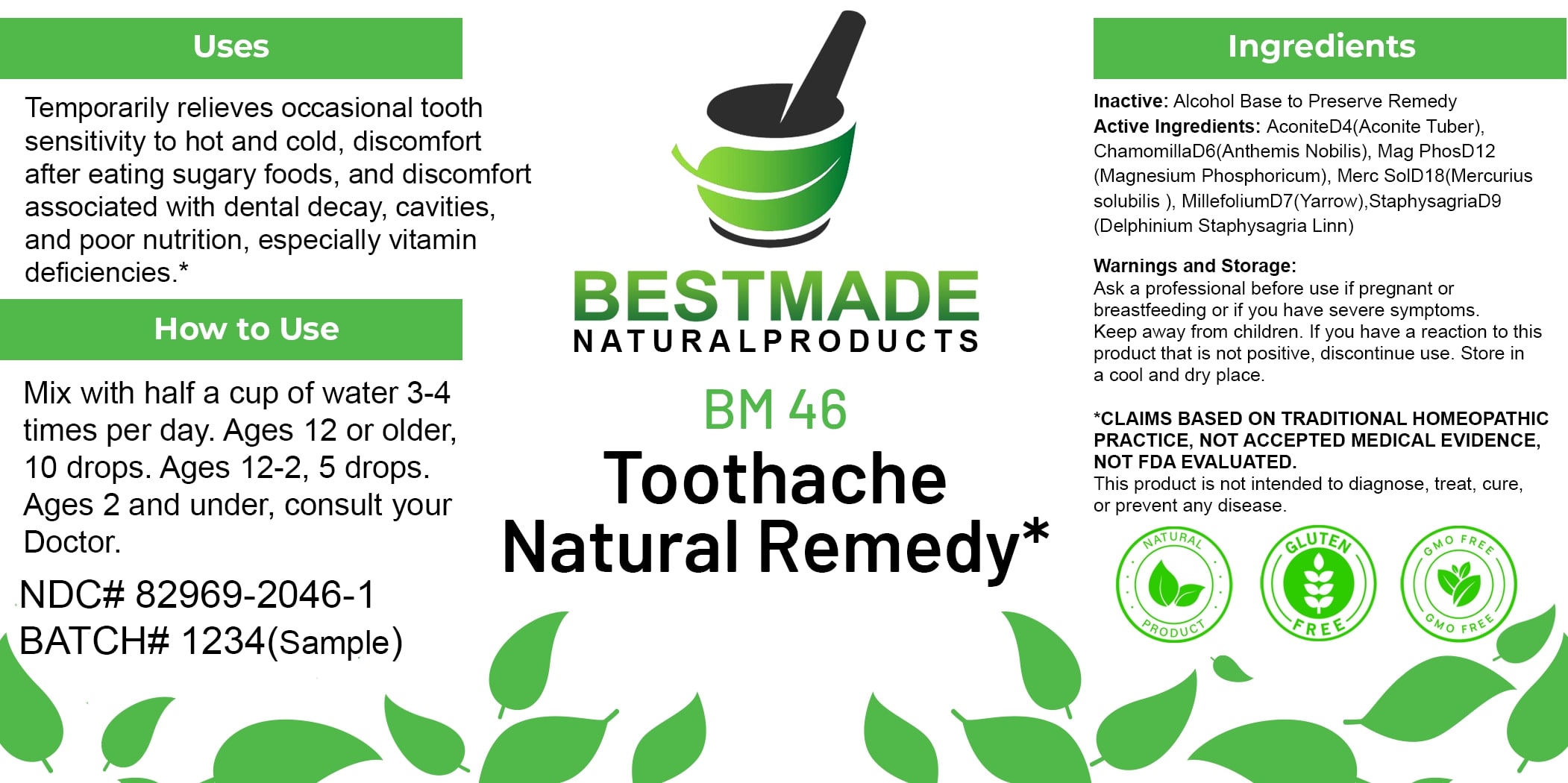 DRUG LABEL: Bestmade Natural Products BM46
NDC: 82969-2046 | Form: LIQUID
Manufacturer: Bestmade Natural Products
Category: homeopathic | Type: HUMAN OTC DRUG LABEL
Date: 20250123

ACTIVE INGREDIENTS: CHAMAEMELUM NOBILE 30 [hp_C]/30 [hp_C]; ACHILLEA MILLEFOLIUM 30 [hp_C]/30 [hp_C]; ACONITUM NAPELLUS 30 [hp_C]/30 [hp_C]; DELPHINIUM STAPHISAGRIA SEED 30 [hp_C]/30 [hp_C]; MERCURIUS SOLUBILIS 30 [hp_C]/30 [hp_C]; MAGNESIUM PHOSPHATE, DIBASIC TRIHYDRATE 30 [hp_C]/30 [hp_C]; ATROPA BELLADONNA 30 [hp_C]/30 [hp_C]
INACTIVE INGREDIENTS: ALCOHOL 30 [hp_C]/30 [hp_C]

BM46

DOSAGE AND ADMINISTRATION

How to Use

Mix with half a cup of water 3-4 times per day. Ages 12 or older, 10 drops. Ages 12-2, 5 drops. Ages 2 and under, consult your Doctor.

INACTIVE INGREDIENT

Ingredients

Inactive: Alcohol Base to Preserve Remedy

ACTIVE INGREDIENT

Active Ingredients: Aconite D4 (Aconite Tuber), Chamomilla D6 (Anthemis Nobilis), Mag Phos D12 (Magnesium Phosphoricum), Merc Sol D18 (Mercurius solubilis), Millefolium D7 (Yarrow), Staphysagria D9 (Delphinium Staphysagria Linn)

Uses

Temporarily relieves occasional tooth sensitivity to hot and cold, discomfort after eating sugary foods, and discomfort associated with dental decay, cavities, and poor nutrition, especially vitamin deficiencies.*

*CLAIMS BASED ON TRADITIONAL HOMEOPATHIC PRACTICE, NOT ACCEPTED MEDICAL EVIDENCE, NOT FDA EVALUATED.

This product is not intended to diagnose, treat, cure, or prevent any disease.

Uses

Temporarily relieves occasional tooth sensitivity to hot and cold, discomfort after eating sugary foods, and discomfort associated with dental decay, cavities, and poor nutrition, especially vitamin deficiencies.*

*CLAIMS BASED ON TRADITIONAL HOMEOPATHIC PRACTICE, NOT ACCEPTED MEDICAL EVIDENCE, NOT FDA EVALUATED.

This product is not intended to diagnose, treat, cure, or prevent any disease.

KEEP OUT OF REACH OF CHILDREN

Warnings and Storage:

Ask a professional before use if pregnant or breastfeeding or if you have severe symptoms. Keep away from children. If you have a reaction to this product that is not positive, discontinue use. Store in a cool and dry place.

Warnings and Storage:

Ask a professional before use if pregnant or breastfeeding or if you have severe symptoms. Keep away from children. If you have a reaction to this product that is not positive, discontinue use. Store in a cool and dry place.

*CLAIMS BASED ON TRADITIONAL HOMEOPATHIC PRACTICE, NOT ACCEPTED MEDICAL EVIDENCE, NOT FDA EVALUATED.

This product is not intended to diagnose, treat, cure, or prevent any disease.

Entire package label